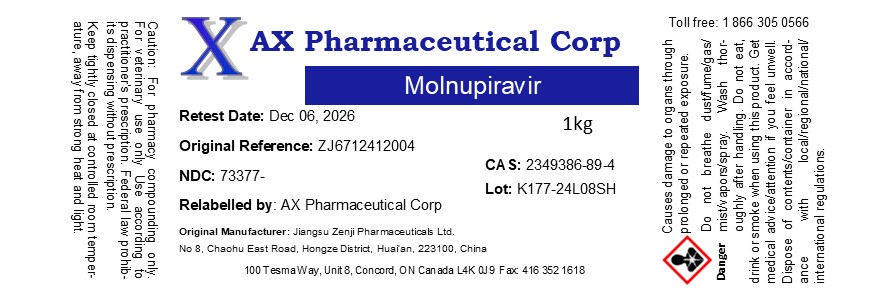 DRUG LABEL: Molnupiravir
NDC: 73377-332 | Form: POWDER
Manufacturer: AX Pharmaceutical Corp
Category: other | Type: BULK INGREDIENT - ANIMAL DRUG
Date: 20250826

ACTIVE INGREDIENTS: MOLNUPIRAVIR 1 g/1 g

Molnupiravir